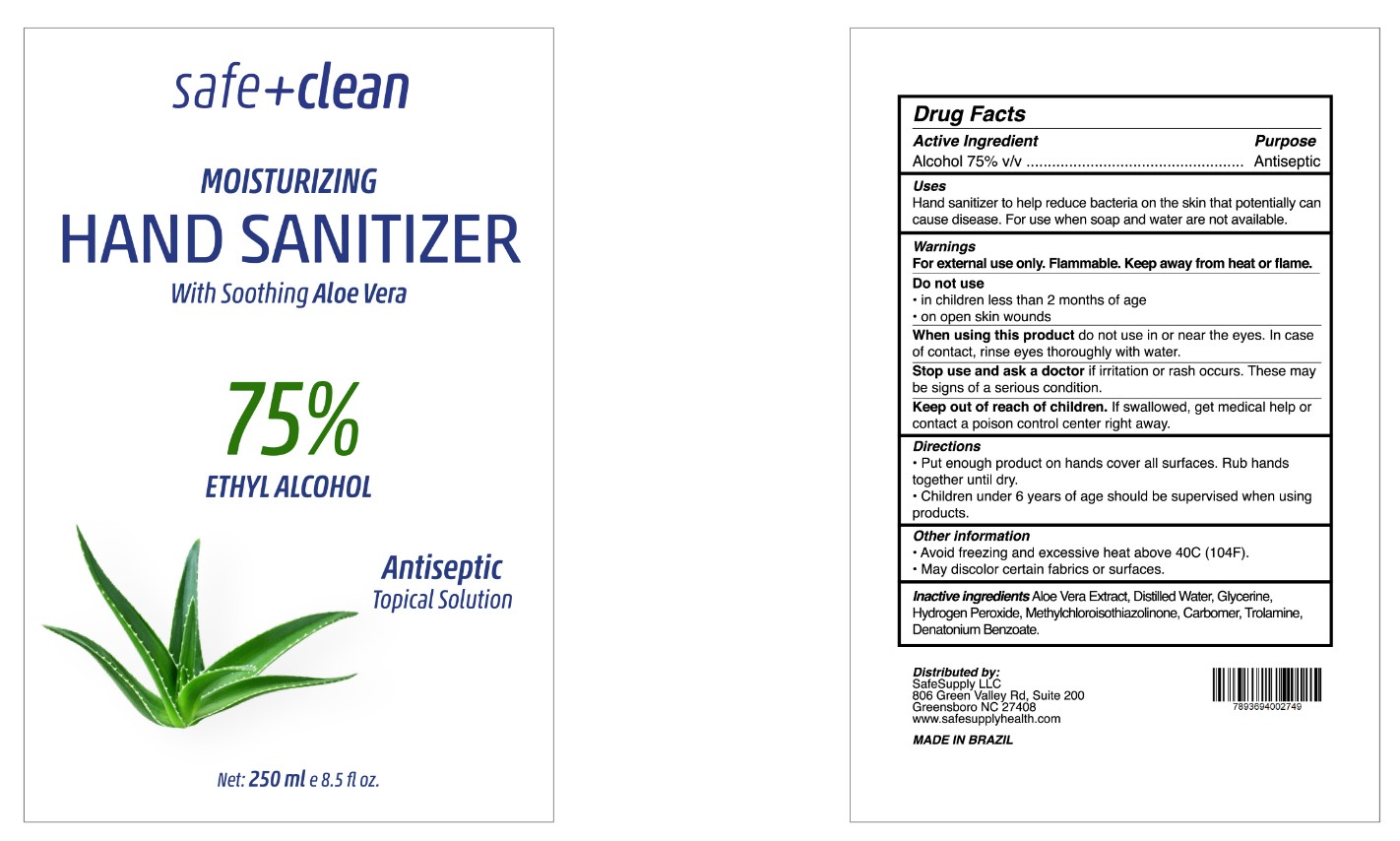 DRUG LABEL: Safe and Clean
NDC: 79990-111 | Form: GEL
Manufacturer: SNC Industria de Cosmeticos Ltda
Category: otc | Type: HUMAN OTC DRUG LABEL
Date: 20200807

ACTIVE INGREDIENTS: ALCOHOL 75 mL/100 mL
INACTIVE INGREDIENTS: METHYLCHLOROISOTHIAZOLINONE; CARBOMER HOMOPOLYMER, UNSPECIFIED TYPE; TROLAMINE; ALOE VERA LEAF; DENATONIUM BENZOATE; GLYCERIN; HYDROGEN PEROXIDE; WATER

SNC Industria-SafeSupply Sanitizer GEL

Active Ingredient(s)

Alcohol 75% v/v. Purpose: Antiseptic

Purpose

Antiseptic, Hand Sanitizer

Use

Hand Sanitizer to help reduce bacteria that potentially can cause disease. For use when soap and water are not available.

Warnings

For external use only. Flammable. Keep away from heat or flame

Do not use

- in children less than 2 months of age
- on open skin wounds

When using this product keep out of eyes, ears, and mouth. In case of contact with eyes, rinse eyes thoroughly with water.
Stop use and ask a doctor if irritation or rash occurs. These may be signs of a serious condition.
Keep out of reach of children. If swallowed, get medical help or contact a Poison Control Center right away.

Stop use and ask a doctor if irritation or rash occurs. These may be signs of a serious condition.

Keep out of reach of children. If swallowed, get medical help or contact a Poison Control Center right away.

Directions

- Place enough product on hands to cover all surfaces. Rub hands together until dry.
- Supervise children under 6 years of age when using this product to avoid swallowing.

Other information

Avoid freezing and excessive heat above 40C (104F)

May discolor certain fabrics or surfaces

Inactive ingredients

aloe vera extract, glycerin, hydrogen peroxide, carbomer, methylchloroisothiazolinone, trolamine, water, denatonium benzoate

Package Label - Principal Display Panel

250 mL NDC: 79990-111-12